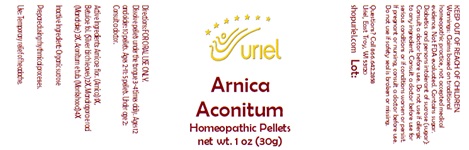 DRUG LABEL: Arnica Aconitum
NDC: 48951-1103 | Form: PELLET
Manufacturer: Uriel Pharmacy Inc.
Category: homeopathic | Type: HUMAN OTC DRUG LABEL
Date: 20251111

ACTIVE INGREDIENTS: ARNICA MONTANA FLOWER 1 [hp_X]/1 1; BETULA PUBESCENS LEAF 2 [hp_X]/1 1; MANDRAGORA OFFICINARUM ROOT 2 [hp_X]/1 1; ACONITUM NAPELLUS 4 [hp_X]/1 1
INACTIVE INGREDIENTS: SUCROSE

Arnica Aconitum

INDICATIONS AND USAGE

Directions: FOR ORAL USE ONLY.

DOSAGE AND ADMINISTRATION

Dissolve pellets under the tongue 3-4 times daily. Ages 12 and older: 10 pellets. Ages 2-11: 5 pellets. Under age 2: Consult a doctor.

Active Ingredients: Arnica e flor. (Arnica) 1X,
Betula e fol. (Silver birch leaves) 2X, Mandragora e rad. (Mandrake) 2X, Aconitum e tub. (Monkshood) 4X

Inactive Ingredient: Organic sucrose

Prepared using rhythmical processes.

PURPOSE

Use: Temporary relief of headache.

KEEP OUT OF REACH OF CHILDREN.

WARNINGS

Warnings: Claims based on traditional homeopathic practice, not accepted medical evidence. Not FDA evaluated. Contains sugar. Diabetics and persons intolerant of sucrose (sugar): Consult a doctor before use. Do not use if allergic to any ingredient. Consult a doctor before use for serious conditions or if conditions worsen or persist. If pregnant or nursing, consult a doctor before use. Do not use if safety seal is broken or missing.

Questions? Call 866.642.2858
Uriel, East Troy, WI 53120
shopuriel.com